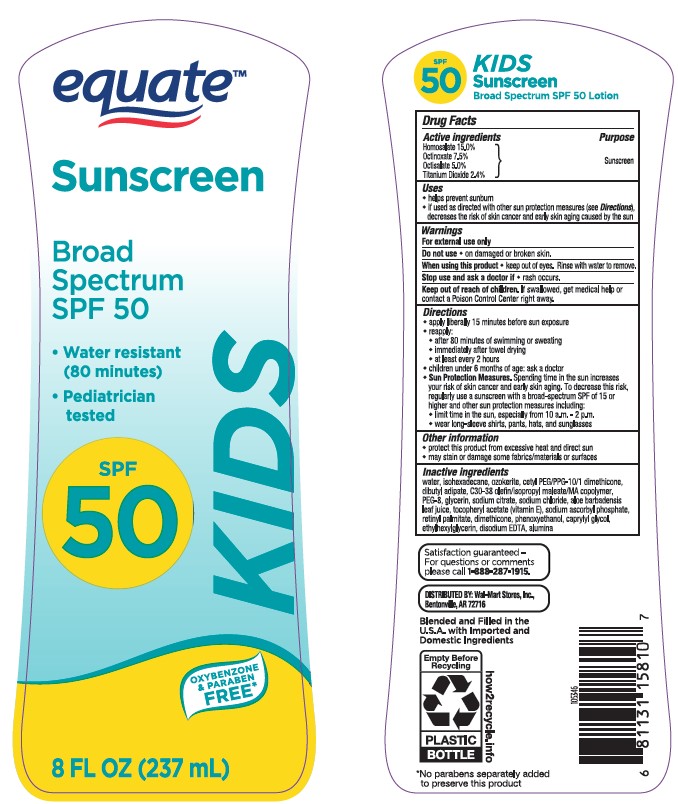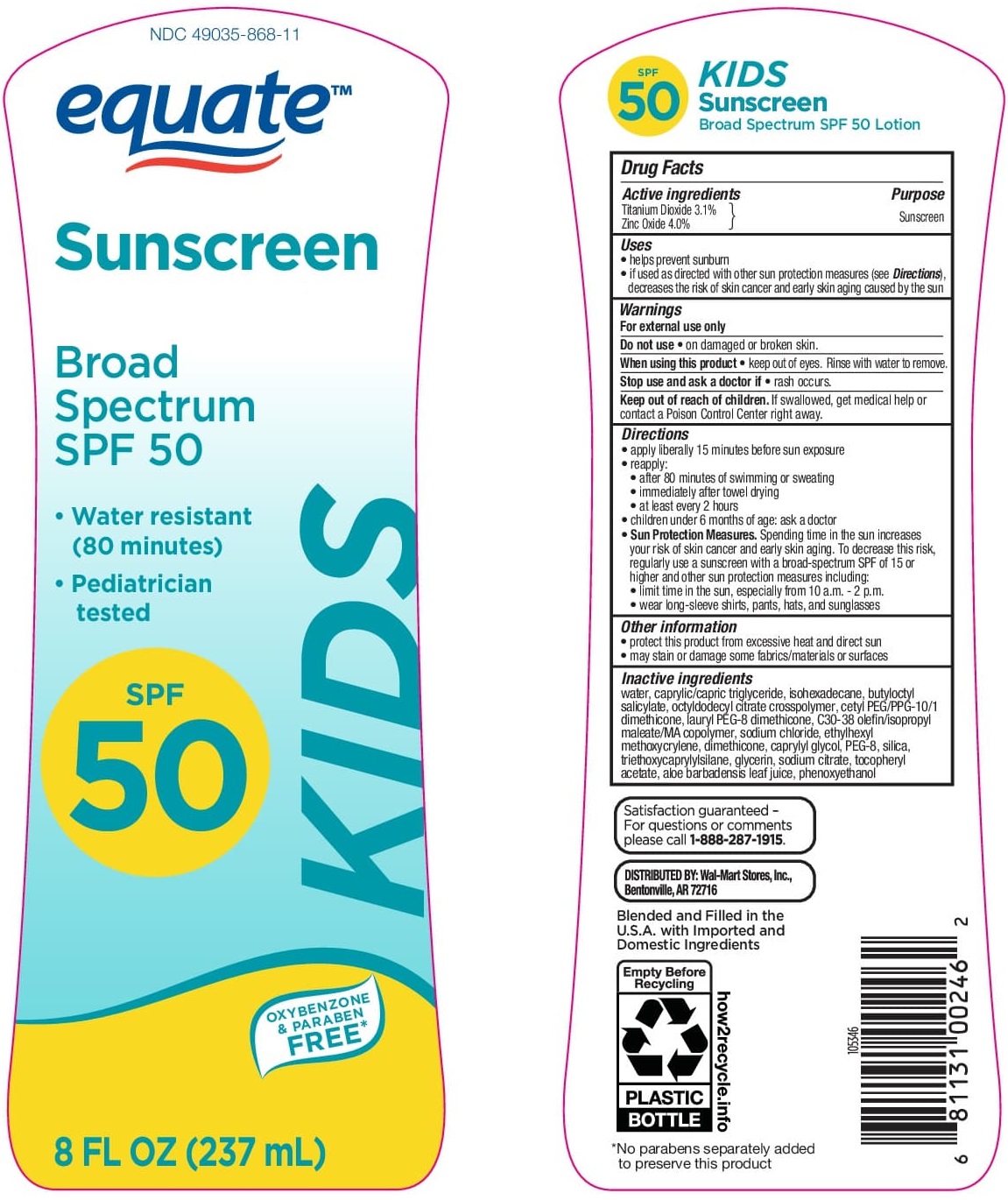 DRUG LABEL: Equate Sunscreen SPF 50 KIDS
NDC: 49035-868 | Form: LOTION
Manufacturer: WAL-MART STORES INC
Category: otc | Type: HUMAN OTC DRUG LABEL
Date: 20241016

ACTIVE INGREDIENTS: TITANIUM DIOXIDE 31 mg/1 mL; ZINC OXIDE 40 mg/1 mL
INACTIVE INGREDIENTS: OCTYLDODECYL CITRATE CROSSPOLYMER; POLYETHYLENE GLYCOL 4000; WATER; MEDIUM-CHAIN TRIGLYCERIDES; ISOHEXADECANE; BUTYLOCTYL SALICYLATE; SODIUM CITRATE; CETYL PEG/PPG-10/1 DIMETHICONE (HLB 5); LAURYL PEG/PPG-18/18 METHICONE; .ALPHA.-TOCOPHEROL ACETATE; SODIUM CHLORIDE; ETHYLHEXYL METHOXYCRYLENE; DIMETHICONE; CAPRYLYL GLYCOL; SILICON DIOXIDE; TRIETHOXYCAPRYLYLSILANE; GLYCERIN; ALOE VERA LEAF; PHENOXYETHANOL

Equate Sunscreen SPF 50 KIDS Broad Spectrum Lotion

Active Ingredients

Titanium Dioxide 3.1%
Zinc Oxide 4.0%

Purpose

Sunscreen

Uses

• helps prevent sunburn
• if used as directed with other sun protection measures (see Directions), decreases the risk of skin cancer and early skin aging caused by the sun

Warnings

For external use only
Do not use • on damaged or broken skin.
When using this product • keep out of eyes. Rinse with water to remove.

Stop use and ask a doctor if

• rash occurs.

Keep out of reach of children

If swallowed, get medical help or contact a Poison Control Center right away.

Directions

• apply liberally 15 minutes before sun exposure
• reapply:
• after 80 minutes of swimming or sweating
• immediately after towel drying
• at least every 2 hours
• children under 6 months of age: ask a doctor
• Sun Protection Measures. Spending time in the sun increases your risk of skin cancer and early skin aging. To decrease this risk, regularly use a sunscreen with a broad-spectrum SPF of 15 or higher and other sun protection measures including:
• limit time in the sun, especially from 10 a.m. - 2 p.m.
• wear long-sleeve shirts, pants, hats, and sunglasses

Other information

• protect this product from excessive heat and direct sun
• may stain or damage some fabrics/materials or surfaces

Inactive Ingredients

water, caprylic/capric triglyceride, isohexadecane, butyloctyl salicylate, octyldodecyl citrate crosspolymer, cetyl PEG/PPG-10/1 dimethicone, lauryl PEG-8 dimethicone, C30-38 olefin/isopropyl maleate/MA copolymer, sodium chloride, ethylhexyl methoxycrylene, dimethicone, caprylyl glycol, PEG-8, silica, triethoxycaprylylsilane, glycerin, sodium citrate, tocopheryl acetate, aloe barbadensis leaf juice, phenoxyethanol.

PACKAGE LABEL

Equate Sunscreen SPF 50 KIDS Broad Spectrum Lotion